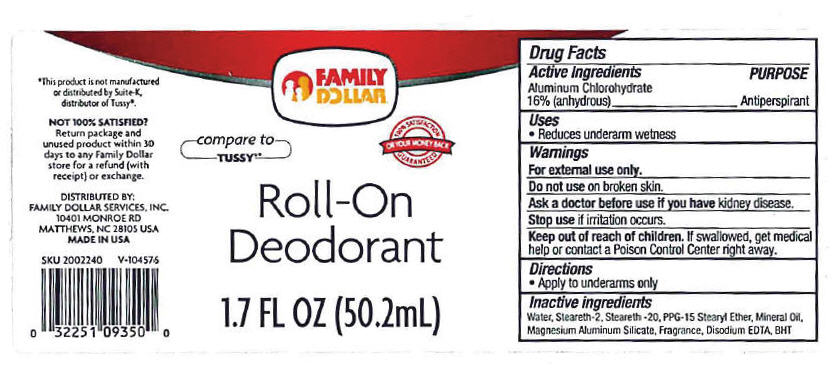 DRUG LABEL: Family Dollar Roll-On Deodorant
NDC: 55319-240 | Form: LOTION
Manufacturer: Family Dollar Services,Inc.
Category: otc | Type: HUMAN OTC DRUG LABEL
Date: 20140512

ACTIVE INGREDIENTS: Aluminum Chlorohydrate 160 mg/1 mL
INACTIVE INGREDIENTS: Water; Edetate Disodium; Magnesium Aluminum Silicate; Mineral Oil; PPG-15 Stearyl Ether; Steareth-20; Steareth-2; Butylated Hydroxytoluene

Family Dollar® Roll-On Deodorant

Drug Facts

Active Ingredients

Aluminum Chlorohydrate 16 % (Anhydrous)

Purpose

Antiperspirant

Uses

Reduces underarm wetness

Warnings

For external use only.

Do not use on broken skin

Ask a doctor before use if you have kidney disease.

Stop use if irritation occurs.

Keep out of reach of children. If swallowed, get medical help or contact a Poison Control Center right away.

Directions

Apply to underarms only

Inactive Ingredients

Water
Steareth-2
Steareth-20
PPG-15 Stearyl Ether
Mineral Oil
Magnesium Aluminum Silicate
Fragrance
Disodium EDTA
BHT

DISTRIBUTED BY:
FAMILY DOLLAR SERVICES, INC.
10401 MONROE RD
MATTHEWS, NC 28105 USA

PRINCIPAL DISPLAY PANEL - 50.2 mL Bottle Label

FAMILY
DOLLAR®

100% SATISFACTION
OR YOUR MONEY BACK
GUARANTEED

compare to
TUSSY®*

Roll-On
Deodorant

1.7 FL OZ (50.2mL)